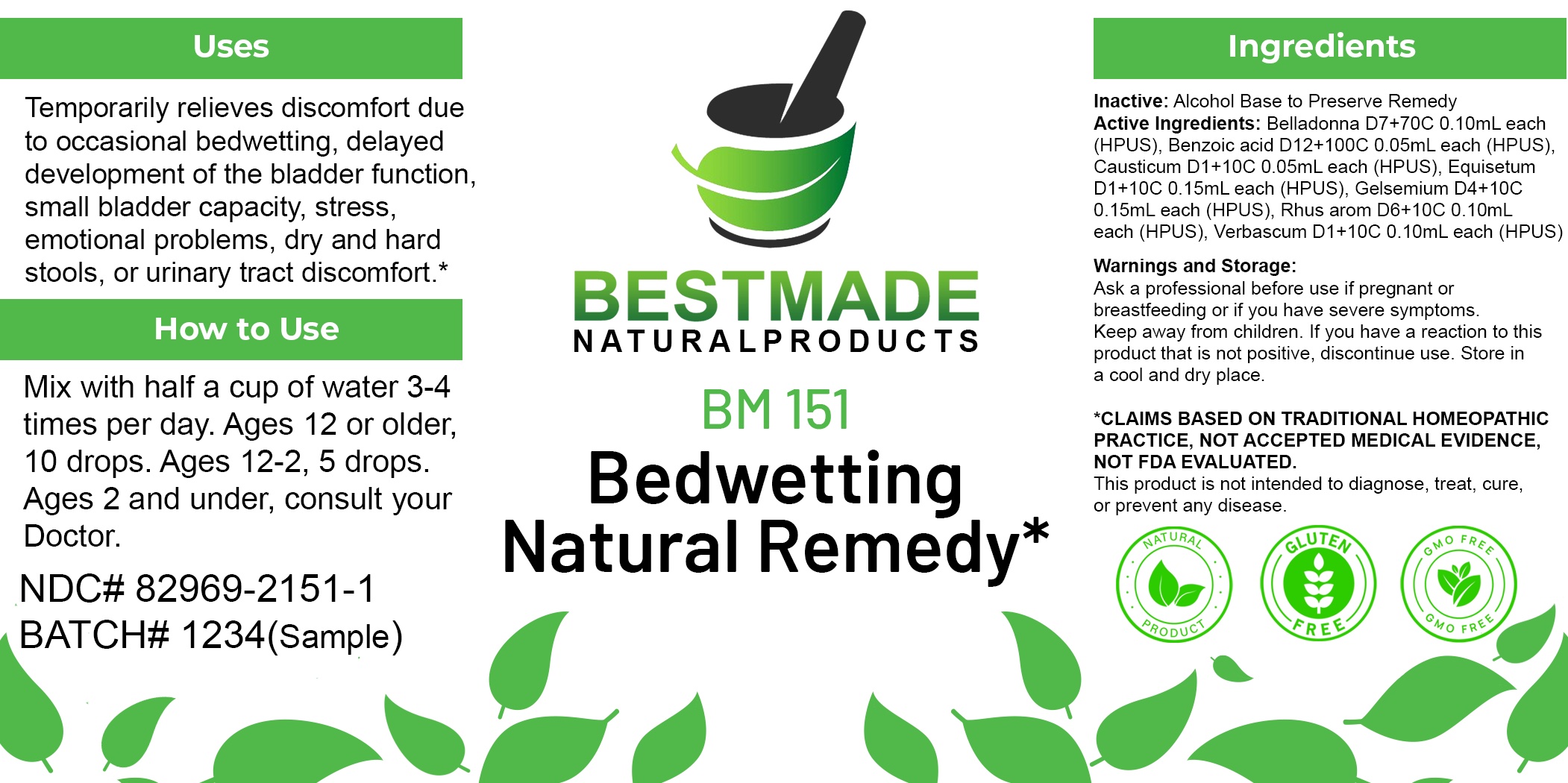 DRUG LABEL: Bestmade Natural Products BM151
NDC: 82969-2151 | Form: LIQUID
Manufacturer: Bestmade Natural Products
Category: homeopathic | Type: HUMAN OTC DRUG LABEL
Date: 20250218

ACTIVE INGREDIENTS: GELSEMIUM SEMPERVIRENS ROOT 30 [hp_C]/30 [hp_C]; VERBASCUM THAPSUS 30 [hp_C]/30 [hp_C]; ATROPA BELLADONNA 30 [hp_C]/30 [hp_C]; BENZOIC ACID 30 [hp_C]/30 [hp_C]; RHUS AROMATICA ROOT BARK 30 [hp_C]/30 [hp_C]; CAUSTICUM 30 [hp_C]/30 [hp_C]; EQUISETUM HYEMALE 30 [hp_C]/30 [hp_C]
INACTIVE INGREDIENTS: ALCOHOL 30 [hp_C]/30 [hp_C]

BM151

DOSAGE AND ADMINISTRATION

How to Use

Mix with half a cup of water 3-4 times per day. Ages 12 or older, 10 drops. Ages 12-2, 5 drops. Ages 2 and under, consult your Doctor.

Inactive:

Alcohol Base to Preserve Product

ACTIVE INGREDIENT

Active Ingredients: Belladonna, Benzoic acid, Causticum, Equisetum, Gelsemium, Rhus arom, Verbascum

Uses

Temporarily relieves discomfort due to occasional bedwetting, delayed development of the bladder function, small bladder capacity, stress, emotional problems, dry and hard stools, or urinary tract discomfort.*

*CLAIMS BASED ON TRADITIONAL HOMEOPATHIC PRACTICE, NOT ACCEPTED MEDICAL EVIDENCE NOT FDA EVALUATED.

This product is not intended to diagnose, treat, cure, or prevent any disease.

Uses

Temporarily relieves discomfort due to occasional bedwetting, delayed development of the bladder function, small bladder capacity, stress, emotional problems, dry and hard stools, or urinary tract discomfort.*

*CLAIMS BASED ON TRADITIONAL HOMEOPATHIC PRACTICE, NOT ACCEPTED MEDICAL EVIDENCE NOT FDA EVALUATED.

This product is not intended to diagnose, treat, cure, or prevent any disease.

KEEP OUT OF REACH OF CHILDREN

Warnings and Storage:

Ask a professional before use if pregnant or breastfeeding or if you have severe symptoms. Keep away from children. If you have a reaction to this product that is not positive, discontinue use. Store in a cool and dry place.

Warnings and Storage:

Ask a professional before use if pregnant or breastfeeding or if you have severe symptoms. Keep away from children. If you have a reaction to this product that is not positive, discontinue use. Store in a cool and dry place.

*CLAIMS BASED ON TRADITIONAL HOMEOPATHIC PRACTICE, NOT ACCEPTED MEDICAL EVIDENCE NOT FDA EVALUATED.

This product is not intended to diagnose, treat, cure, or prevent any disease.

Entire package label